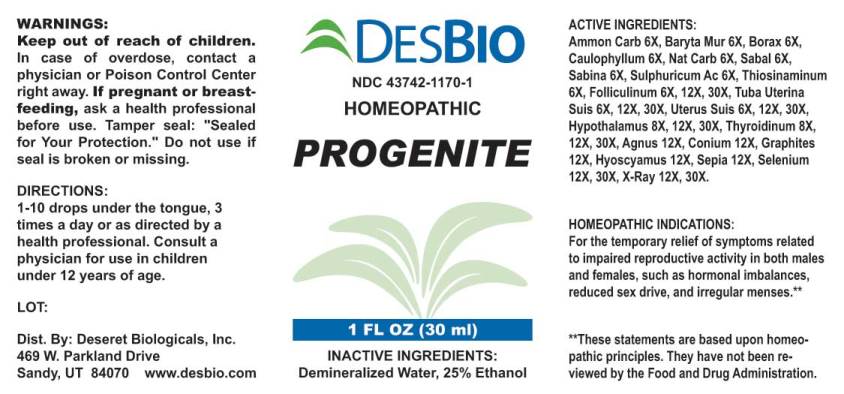 DRUG LABEL: Progenite
NDC: 43742-1170 | Form: LIQUID
Manufacturer: Deseret Biologicals
Category: homeopathic | Type: HUMAN OTC DRUG LABEL
Date: 20231212

ACTIVE INGREDIENTS: AMMONIUM CARBONATE 6 [hp_X]/1 mL; BARIUM CHLORIDE DIHYDRATE 6 [hp_X]/1 mL; SODIUM BORATE 6 [hp_X]/1 mL; CAULOPHYLLUM THALICTROIDES ROOT 6 [hp_X]/1 mL; SODIUM CARBONATE 6 [hp_X]/1 mL; SAW PALMETTO 6 [hp_X]/1 mL; JUNIPERUS SABINA LEAFY TWIG 6 [hp_X]/1 mL; SULFURIC ACID 6 [hp_X]/1 mL; ALLYLTHIOUREA 6 [hp_X]/1 mL; ESTRONE 6 [hp_X]/1 mL; SUS SCROFA FALLOPIAN TUBE 6 [hp_X]/1 mL; SUS SCROFA UTERUS 6 [hp_X]/1 mL; SUS SCROFA HYPOTHALAMUS 8 [hp_X]/1 mL; THYROID 8 [hp_X]/1 mL; CHASTE TREE 12 [hp_X]/1 mL; CONIUM MACULATUM FLOWERING TOP 12 [hp_X]/1 mL; GRAPHITE 12 [hp_X]/1 mL; HYOSCYAMUS NIGER 12 [hp_X]/1 mL; SEPIA OFFICINALIS JUICE 12 [hp_X]/1 mL; SELENIUM 12 [hp_X]/1 mL; ALCOHOL, X-RAY EXPOSED (1000 RAD) 12 [hp_X]/1 mL
INACTIVE INGREDIENTS: WATER; ALCOHOL

Drug Facts:

ACTIVE INGREDIENTS:

Ammonium Carbonicum 6X, Baryta Muriatica 6X, Borax 6X, Caulophyllum Thalictroides 6X, Natrum Carbonicum 6X, Sabal Serrulata 6X, Sabina 6X, Sulphuricum Acidum 6X, Thiosinaminum 6X, Folliculinum 6X, 12X, 30X, Tuba Uterina Suis 6X, 12X, 30X, Uterus Suis 6X, 12X, 30X, Hypothalamus (Suis) 8X, 12X, 30X, Thyroidinum (Suis) 8X, 12X, 30X, Agnus Castus 8X, 12X, 30X, Conium Maculatum 12X, Graphites 12X, Hyoscyamus Niger 12X, Sepia 12X, Selenium Metallicum 12X, 30X, X-Ray 12X, 30X.

HOMEOPATHIC INDICATIONS:

For temporary relief of symptoms related to impaired reproductive activity in both males and females, such as hormonal imbalances, reduced sex drive, and irregular menses.**

**These statements are based upon traditional homeopathic principles. They have not been reviewed by the Food and Drug Administration.

WARNINGS:

Keep out of reach of children. In case of overdose, contact physician or a Poison Control Center right away.

If pregnant or breast-feeding, ask a health professional before use.

Tamper seal: "Sealed for Your Protection." Do not use if seal is broken or missing.

Keep out of reach of children. In case of overdose, contact physician or a Poison Control Center right away.

DIRECTIONS:

1-10 drops under the tongue, 3 times a day or as directed by a health professional. Consult a physician for use in children under 12 years of age.

HOMEOPATHIC INDICATIONS:

For temporary relief of symptoms related to impaired reproductive activity in both males and females, such as hormonal imbalances, reduced sex drive, and irregular menses.**

**These statements are based upon traditional homeopathic principles. They have not been reviewed by the Food and Drug Administration.

INACTIVE INGREDIENTS:

Demineralized Water, 25% Ethanol

QUESTIONS:

Dist. By: Deseret Biologicals, Inc.
469 W. Parkland Drive
Sandy, UT 84070 www.desbio.com

PACKAGE LABEL DISPLAY:

DESBIO
NDC 43742-1170-1
HOMEOPATHIC
PROGENITE
1 FL OZ (30 ml)